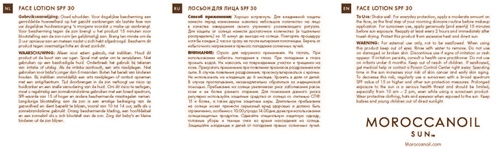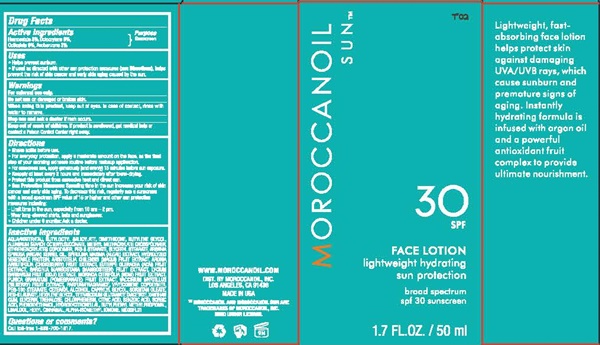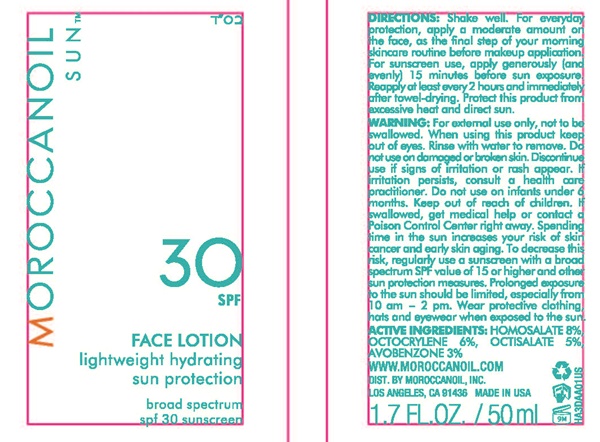 DRUG LABEL: MOROCCAN Lightweight Hydrating Sun Protection SPF 30
NDC: 54111-133 | Form: LOTION
Manufacturer: Bentley Laboratories, LLC
Category: otc | Type: HUMAN OTC DRUG LABEL
Date: 20181219

ACTIVE INGREDIENTS: AVOBENZONE 1.5 g/50 mL; HOMOSALATE 4 g/50 mL; OCTISALATE 2.5 g/50 mL; OCTOCRYLENE 3 g/50 mL
INACTIVE INGREDIENTS: WATER; BUTYLOCTYL SALICYLATE; DIMETHICONE; BUTYLENE GLYCOL; ALUMINUM STARCH OCTENYLSUCCINATE; OCTENYLSUCCINIC ACID; METHYL METHACRYLATE/GLYCOL DIMETHACRYLATE CROSSPOLYMER; STYRENE/ACRYLAMIDE COPOLYMER (MW 500000); PEG-8 STEARATE; GLYCERYL MONOSTEARATE; ARGAN OIL; ARTHROSPIRA MAXIMA; HYDROGENATED SOYBEAN OIL; ARISTOTELIA CHILENSIS FRUIT; ARONIA MELANOCARPA FRUIT JUICE; ACAI; GARCINIA MANGOSTANA FRUIT; LYCIUM BARBARUM FRUIT; NONI FRUIT; POMEGRANATE; BILBERRY; VINYLPYRROLIDONE/EICOSENE COPOLYMER; PEG-100 STEARATE; CETOSTEARYL ALCOHOL; CAPRYLYL GLYCOL; SORBITAN MONOOLEATE; PEG-8 LAURATE; HEXYLENE GLYCOL; TETRASODIUM GLUTAMATE DIACETATE; XANTHAN GUM; GLYCERIN; TREHALOSE; CHLORPHENESIN; CITRIC ACID MONOHYDRATE; BENZOIC ACID; SORBIC ACID; PHENOXYETHANOL; HYDROXYCITRONELLAL; BUTYLPHENYL METHYLPROPIONAL; LINALOOL, (+)-; .ALPHA.-HEXYLCINNAMALDEHYDE; ISOMETHYL-.ALPHA.-IONONE

MOROCCANOIL Lightweight Hydrating Sun Protection SPF 30 133

Drug Facts Active Ingredients

Homosalate 8%, Octocrylene 6%

Octisalate 5%, Avobenzone 3.0%

Purpose

Sunscreen

Uses

- Helps prevent sunburn
- If used as directed with other sun protection measures (see Directions), helps prevent the risk of skin cancer and early skin aging caused by the sun.

Warnings

For external use only.

Do not use on damaged or broken skin.

When using this product, keep out of eyes. In case of contact, rinse with water to remove.

Stop use and ask a doctor if rash occurs.

Keep out of reach of children. If product is swallowed, get medical help or contact a Poison Control Center right away.

Directions

- Shake bottle before use.
- For everyday protection, apply a moderate amount on the face, as the final step of your morning skincare routine before makeup application.
- For sunscreen use, apply generously (and evenly) 15 minutes before sun exposure.
- Reapply at least every 2 hours and immediately after towel-drying.
- Protect this product from excessive heat and direct sun.
- Sun Protection Measures: Spending time in the sun increases your risk of skin cancer and early skin aging. To decrease this risk, regularly use a sunscreen with a broad spectrum SPF value of 15 or higher and other sun protection measures including:
- Limit time in the sun, especially from 10 am - 2 pm.
- Wear long-sleeved shirts, hat and sunglasses.
- Children under 6 months: Ask a doctor.

Inactive Ingredients

AQUA/WATER/EAU, BUTYLOCTYL SALICYLATE, DIMETHICONE, BUTYLENE GLYCOL, ALUMINUM STARCH OCTENYLSUCCINATE, METHYL METHACRYLATE CROSSPOLYMER, STYRNEN/ACRYLATES COPOLYMER, PEG-8 STEARATE, GLYCERYL STEARATE, ARGANIA SPINOSA (ARGAN) KERNAL OIL, SPIRULINA MAXIMA (ALGAE) EXTRACT, HYDROLYZED VEGETABLE PROTEIN, ARISTOTELIA CHILENSIS (MAQUI) FRUIT EXTRACT, ARONIA ARBUTIFOLIA (CHOKEBERRY) FRUIT EXTRACT, EUTWRPE OLERACEA (ACAI) FRUIT EXTRACT, GARCINIA MANGOSTANA (MANGOSTEEN) FRUIT EXTRACT, LYCIUM BARBARUM FRUIT Z9GOJI)EXTRACT, MORINDA CITRIFOLIA (NONI) FRUIT EXTRACT, PUNICA GRANATUM (POMEGRANATE)FRUIT EXTRACT, VACCINIUM MYRILLUS (BILBERRY) FRUIT EXTRACT, PARFUM/FRAGRANCE, VP/EICOSENE COPOLYMER, PEG-100 STEARATE, CETEARYL ALCOHOL, CAPRYLYL GLYCOL, SORBITAN OLEATE, PEG-8 LAURATE, HEXYLENE GLYCOL, TETRASODIUM GLUTAMATE DIACETATE, XANTHAN GUM, GLYCERIN, TREHALOSE, CHLORPHENESIN, CITRIC ACID, BENZONIC ACID, SORBIC ACID, PHENOXETHANOL, HYDROXYCITRONELLAL, BUTYLPHENYL METHYLPROPIONAL, LINALOOL, HEXYL CINNAMAL, ALPHA-ISOMETHYL IONONE. M030FL01

Questions or comments?

Call toll-free 1-888-700-1817.

MOROCCANOIL SUN™ 30 SPF

MOROCCANOIL SUN™

30 SPF

FACE LOTION
lightweight hydrating
sun protection

broad spectrum
spf 30 sunscreen

1.7 FL.OZ./50 ml

Lightweight, fast-absorbing face lotion helps protect skin against damaging UVA/UVB rays, which cause sunburn and premature signs of aging. Instantly hydrating formula is infused with argan oil and a powerful antioxidant fruit complex to provide ultimate nourishment.

WWW.MOROCCANOIL.COM
DIST. BY MOROCCANOIL, INC.
LOS ANGELES, CA 91436
MADE IN USA

™MOROCCANOIL AND MOROCCANOIL SUN ARE
TRADEMARKS OF MOROCCANOIL, INC.
USED UNDER LICENSE